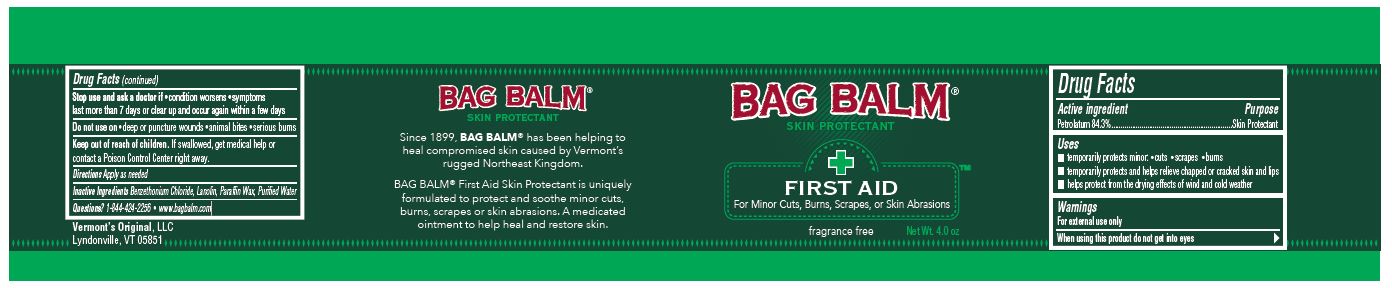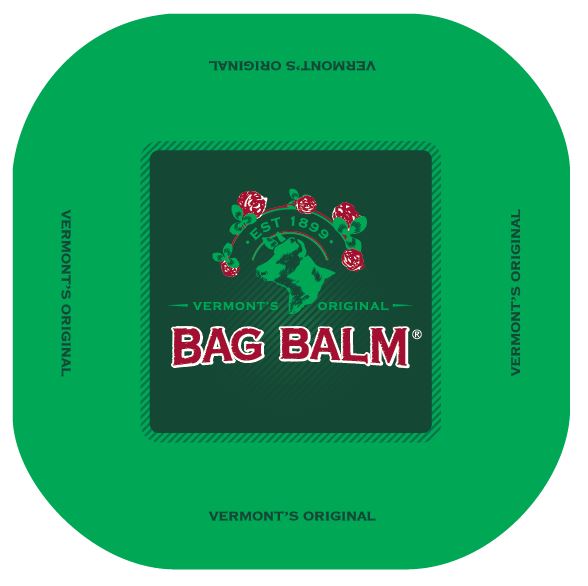 DRUG LABEL: BAG BALM Skin Protectant
NDC: 69845-031 | Form: OINTMENT
Manufacturer: VERMONT`S ORIGINAL, LLC
Category: otc | Type: HUMAN OTC DRUG LABEL
Date: 20170714

ACTIVE INGREDIENTS: Petrolatum 84.3 g/100 g
INACTIVE INGREDIENTS: Benzethonium Chloride; Lanolin; Paraffin; Water

Drug Facts

ACTIVE INGREDIENT

Active ingredient | Purpose
Petrolatum 84.3% | Skin Protectant

Uses

- temporarily protects minor: • cuts • scrapes • burns
- temporarily protects and helps relieve chapped or cracked skin and lips
- helps protect from the drying effects of wind and cold weather

Warnings

For external use only

Stop use and ask a doctor if

- condition worsens
- symptoms last more than 7 days or clear up and occur again within a few days

Do not use on

- deep or puncture wounds
- animal bites
- serious burns

Keep out of reach of children.

If swallowed, get medical help or contact a Poison Control Center right away.

DOSAGE AND ADMINISTRATION

Directions Apply as needed

INACTIVE INGREDIENT

Inactive Ingredients Benzethonium Chloride, Lanolin, Paraffin Wax, Purified Water

Questions? 1-844-424-2256 • www.bagbalm.com

PACKAGE LABEL

BAG BALM®
SKIN PROTECTANT
FIRST AID
For Minor Cuts, Burns, Scrapes, or Skin Abrasions
fragrance free
Net Wt. 4.0 oz
Since 1899, BAG BALM® has been helping to heal compromised skin caused by Vermont’s rugged Northeast Kingdom.
BAG BALM® First Aid Skin Protectant is uniquely formulated to protect and soothe minor cuts, burns, scrapes or skin abrasions. A medicated ointment to help heal and restore skin.
Vermont’s Original, LLC
Lyndonville, VT 05851

● EST 1899 ●
VERMONT'S ORIGINAL
BAG BALM®